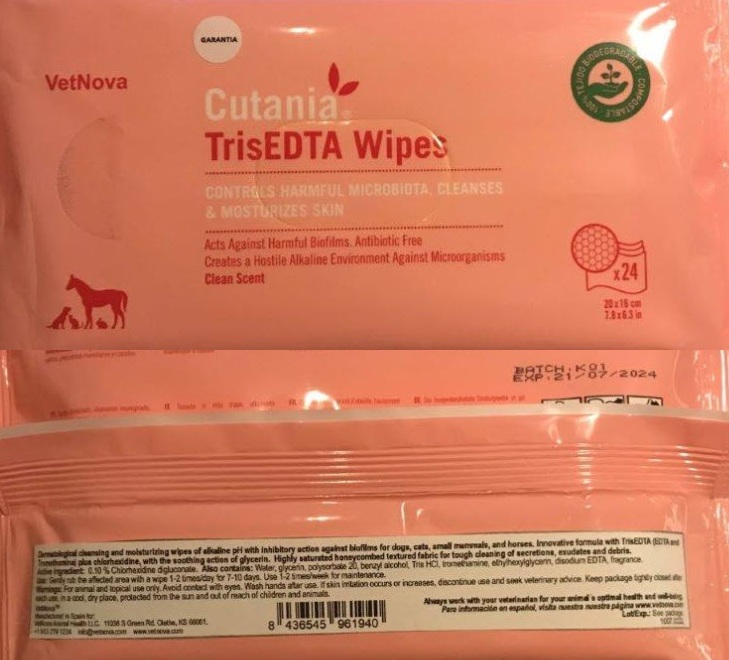 DRUG LABEL: Cutania TrisEDTA  Wipes
NDC: 86145-300 | Form: CLOTH
Manufacturer: Vetnova Animal Health LLC
Category: animal | Type: OTC ANIMAL DRUG LABEL
Date: 20251119

ACTIVE INGREDIENTS: CHLORHEXIDINE GLUCONATE 0.006 mg/1 1
INACTIVE INGREDIENTS: Benzyl Alcohol; EDETATE DISODIUM; Tromethamine; TROMETHAMINE HYDROCHLORIDE; Water

Cutania® TrisEDTA Wipes

INDICATIONS AND USAGE

Dermatological cleansing and moisturizing wipes of alkaline pH with inhibitory action against biofilms for dogs, cats, small mammals, and horses. Innovative formula with TrisEDTA (EDTA and Tromethamine) plus chlorhexidine, with the soothing action of glycerin. Highly saturated honeycombed textured fabric for tough cleaning of secretions, exudates and debris.

Active Ingredient: 0.10 % Chlorhexidine digluconate. Also contains: Water, glycerin, polysorbate 20, benzyl alcohol, Tris HCl, tromethamine, ethylhexylglycerin, disodium EDTA, fragrance.

DOSAGE AND ADMINISTRATION

Use: Gently rub the affected area with a wipe 1-2 times/day for 7-10 days. Use 1-2 times/week for maintenance. Warnings: For animal and topical use only. Avoid contact with eyes. Wash hands after use. If skin irritation occurs or increases, discontinue use and seek veterinary advice. Keep package tightly closed after each use, in a cool, dry place, protected from the sun and out of reach of children and animals.

Always work with your veterinarian for your animal´s optimal health and well-being.

Manufactured in Spain for: VetNova Animal Health LLC. 11036 S Green Rd. Olathe, KS 66061.

+1 913 279 1224 info@vetnova.com www.vetnova.com

NDC 86145-300-01

Cutania Tris EDTA Wipes

PRINCIPAL DISPLAY PANEL - 24 Wipe Pouch

GARANTIA

VetNova

Cutania®
TrisEDTA Wipes

CONTROLS HARMFUL MICROBIOTA, CLEANSES
& MOSTURIZES SKIN

Acts Against Harmful Biofilms. Antibiotic Free
Creates a Hostile Alkaline Environment Against Microorganisms

Clean Scent

100% TEJIDO BIODEGRADABLE
• COMPOSTABLE •

x24

20 x 16 cm
7.8 x 6.3 in